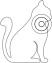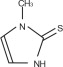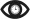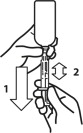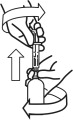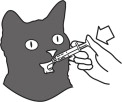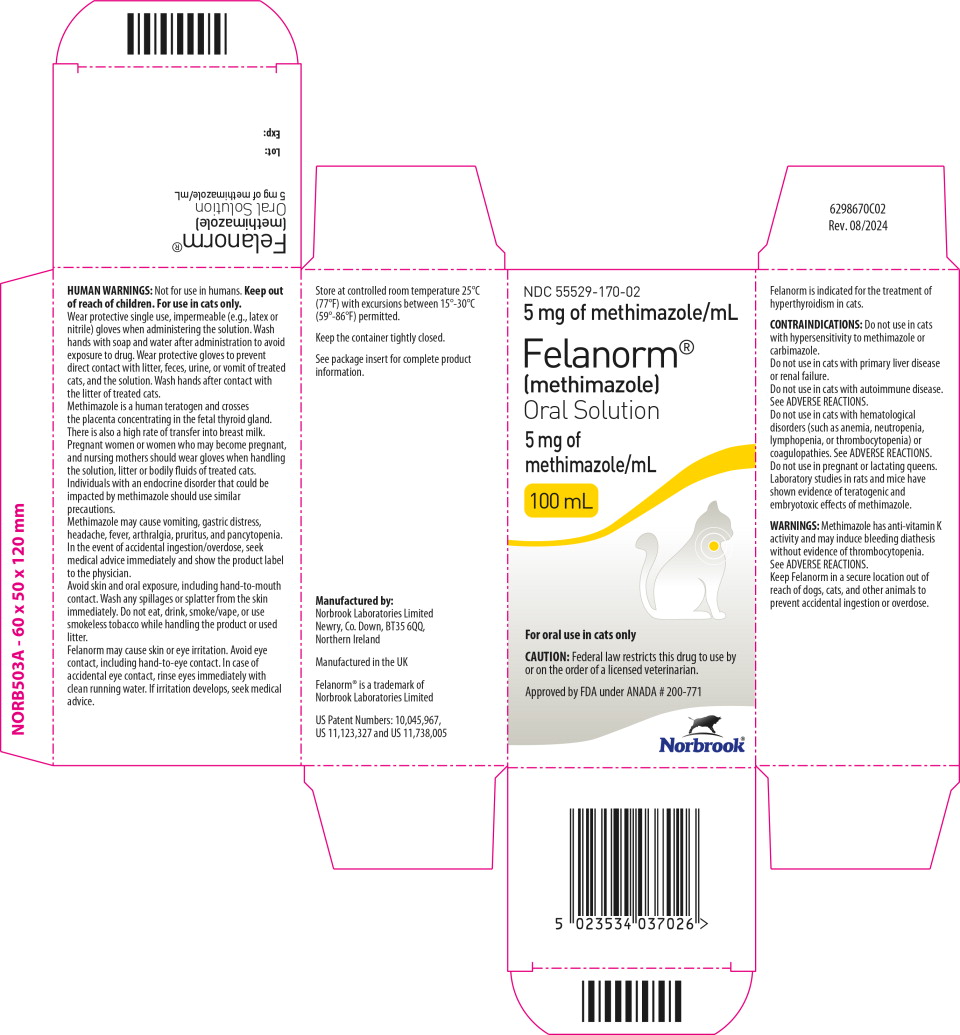 DRUG LABEL: Felanorm
NDC: 55529-170 | Form: SOLUTION
Manufacturer: Norbrook Laboratories Limited
Category: animal | Type: PRESCRIPTION ANIMAL DRUG LABEL
Date: 20250217

ACTIVE INGREDIENTS: METHIMAZOLE 5 mg/1 mL

Felanorm® (methimazole) Oral Solution

For oral use in cats only

CAUTION: Federal law restricts this drug to use by or on the order of a licensed veterinarian.

DESCRIPTION:

Methimazole is a thioureylene antithyroid drug, which inhibits the synthesis of thyroid hormones. Methimazole (1-methylimidazole-2-thiol) is a white, crystalline substance that is freely soluble in water. The chemical formula is C4H6N2S. Molecular weight is 114.16.

Methimazole Chemical Structure:

INDICATION:

Felanorm (methimazole) is indicated for the treatment of hyperthyroidism in cats.

DOSAGE AND ADMINISTRATION:

Always include the Instructions for Preparing a Dose of Felanorm (methimazole) Oral Solution and the Information for Cat Owners with the prescription. The starting dose of Felanorm is 2.5 mg administered every 12 hours. Following 3 weeks of treatment, the dose should be titrated to effect based on individual serum total T4 (TT4) levels and clinical response. Dose adjustments should be made in 2.5 mg increments. The maximum total dosage is 20 mg per day divided, not to exceed 10 mg as a single administration.

Hematology, biochemistry, and TT4 should be evaluated prior to initiating treatment and monitored after 3 weeks and 6 weeks of treatment. Thereafter, bloodwork should be monitored every 3 months and the dose adjusted as necessary. Cats receiving doses greater than 10 mg per day should be monitored more frequently.

The product should be administered orally using the enclosed graduated dosing syringe. The syringe has measurements representing the mg dose of the product. Rinse/clean the oral dosing syringe between uses. (See the Instructions for Preparing a Dose of Felanorm (methimazole) Oral Solution).

CONTRAINDICATIONS:

Do not use in cats with hypersensitivity to methimazole or carbimazole. Do not use in cats with primary liver disease or renal failure.

Do not use in cats with autoimmune disease. See ADVERSE REACTIONS.

Do not use in cats with hematological disorders (such as anemia, neutropenia, lymphopenia, or thrombocytopenia) or coagulopathies. See ADVERSE REACTIONS.

Do not use in pregnant or lactating queens. Laboratory studies in rats and mice have shown evidence of teratogenic and embryotoxic effects of methimazole.

WARNINGS:

Methimazole has anti-vitamin K activity and may induce bleeding diathesis without evidence of thrombocytopenia. See ADVERSE REACTIONS.

Keep Felanorm in a secure location out of reach of dogs, cats, and other animals to prevent accidental ingestion or overdose.

HUMAN WARNINGS:

Not for use in humans. Keep out of reach of children. For use in cats only. Wear protective single use, impermeable (e.g., latex or nitrile) gloves when administering the solution. Wash hands with soap and water after administration to avoid exposure to drug. Wear protective gloves to prevent direct contact with litter, feces, urine, or vomit of treated cats, and the solution. Wash hands after contact with the litter of treated cats.

Methimazole is a human teratogen and crosses the placenta concentrating in the fetal thyroid gland. There is also a high rate of transfer into breast milk. Pregnant women or women who may become pregnant, and nursing mothers should wear gloves when handling the solution, litter or bodily fluids of treated cats. Individuals with an endocrine disorder that could be impacted by methimazole should use similar precautions.

Methimazole may cause vomiting, gastric distress, headache, fever, arthralgia, pruritus, and pancytopenia. In the event of accidental ingestion/overdose, seek medical advice immediately and show the product label to the physician.

Avoid skin and oral exposure, including hand-to-mouth contact. Wash any spillages or splatter from the skin immediately. Do not eat, drink, smoke/vape, or use smokeless tobacco while handling the product or used litter.

Felanorm may cause skin or eye irritation. Avoid eye contact, including hand-to-eye contact. In case of accidental eye contact, rinse eyes immediately with clean running water. If irritation develops, seek medical advice.

PRECAUTIONS:

Use of Felanorm in cats with renal dysfunction should be carefully evaluated. Reversal of hyperthyroidism may be associated with decreased glomerular filtration rate and a decline in renal function, unmasking the presence of underlying renal disease. Due to potentially serious adverse reactions such as hepatopathy, immune-mediated anemia, thrombocytopenia, and agranulocytosis, cats on methimazole therapy should be monitored closely for any sign of illness including anorexia, vomiting, head/facial pruritus or edema, depression/lethargy, weight loss, anemia, skin lesions, diarrhea, fever, or lymphadenopathy. If a cat becomes ill while on Felanorm, the drug should be stopped and appropriate hematological and biochemical testing should be done (see ANIMAL SAFETY and POST APPROVAL EXPERIENCE). Anticoagulants may be potentiated by the anti-vitamin K activity of Felanorm. Concurrent use of phenobarbital may reduce the clinical effectiveness of Felanorm.

A reduction in dose of certain drugs (β-adrenergic blocking agents, digitalis glycosides, and theophylline) may be needed when the patient becomes euthyroid.

Methimazole is known to reduce the hepatic oxidation of benzimidazole anthelmintics (e.g. fenbendazole), leading to increased plasma concentration of these anthelmintics when administered concurrently.

Methimazole caused delayed maturation of the testes in young male cats in the 12-week safety study. See ANIMAL SAFETY. The safety of Felanorm has not been evaluated in male cats intended for breeding.

ADVERSE REACTIONS:

In a US field study with 113 cats, the most common adverse reactions included change in food consumption (increase or decrease), lethargy, vomiting, diarrhea/loose stool, skin lesions, and abnormal vocalization. Three cats were withdrawn early from the study, one due to unmasking of latent renal disease and two due to the development of skin lesions. Over the course of the study, there was a decreasing trend in the mean counts of red blood cells, lymphocytes, neutrophils and monocytes; however, means remained within or near normal ranges for the testing laboratory. In the extended use phase of the US field study with 101 cats, the most common adverse reactions reported in the study above (lethargy, anorexia) were also observed. Additional signs occurring more frequently in the long-term study were:

depression/withdrawn behavior, weight loss, hair coat abnormalities, increased blood urea nitrogen (BUN), weakness, agitation and diarrhea. Most of the adverse reactions reported were mild and transient.

Serum chemistry and hematology results in the extended use study were consistent with the trends noted during the field study. The mean alanine transaminase (ALT) was above the reference range at the first two quarterly visits, but within the normal reference range (10-100 U/L) through the next two quarterly visits.

Mean lymphocyte counts decreased consistently during the study period, to slightly below the reference range (1200-8000 cells/mcL) at the fourth quarterly visit.

Sixteen cats experienced elevated antinuclear antibody (ANA) titers at one or more points during long-term therapy with methimazole, but the significance was not determined. Eighteen cats died or were euthanized during the extended use study, four of which may have been related to methimazole due to the unmasking/acceleration of chronic renal failure. See PRECAUTIONS.

In a foreign field study with 26 cats using a starting dose of 5 mg twice daily (twice the recommended starting dose), one cat was withdrawn due to lethargy, vomiting and facial excoriations. Marked thrombocytopenia was reported in two cats; the platelet count returned to normal in one cat when methimazole tablets were discontinued. Two cats collapsed and died within 12 days of starting methimazole at a dose of 5 mg twice daily. Both cats were reported with lethargy, vomiting, anorexia, and bloody diarrhea; one cat also had pallor.

In a second foreign field study with 78 cats using a starting dose of 2.5 mg twice daily, 4 cats were withdrawn due to suspected adverse reactions to methimazole including anemia, cholangiohepatitis, excoriations, vomiting, lethargy, jaundice, and anorexia. One cat receiving 2.5 mg three times daily collapsed and died after 8 weeks of treatment. Adverse reactions included pallor, anorexia, dehydration, jaundice, bleeding diathesis, and anemia. The most frequently reported adverse reactions included mild, transient, self-limiting vomiting, lethargy, and anorexia.

Foreign Market Experience: The following events were reported voluntarily during post-approval use of methimazole in foreign markets: facial pruritus, self-induced excoriations of the head and neck, generalized lymphadenopathy, thrombocytopenia, hematemesis, epistaxis, and elevation of serum liver enzymes and bilirubin.

If overdosage occurs, stop treatment and give symptomatic and supportive care.

POST APPROVAL EXPERIENCE (revised 2015): The following adverse events are based on voluntary, post approval reporting. Not all adverse events are reported to FDA/CVM. It is not always possible to reliably estimate the adverse event frequency or establish a causal relationship to product exposure using these data. The following adverse events are listed in decreasing order of reporting frequency: Anorexia, vomiting, head/facial pruritus or edema, depression/lethargy, weight loss, anemia, elevated liver enzymes, skin lesions, elevated BUN, diarrhea, and thrombocytopenia. In some reported cases, the patients recovered after adverse signs were recognized, the drug was withdrawn, and veterinary care was applied. In some cases, death (or euthanasia) has been reported as an outcome of the adverse reactions listed above.

CONTACT INFORMATION:

To report suspected adverse drug events, for technical assistance or to obtain a copy of the Safety Data Sheet (SDS), contact Norbrook at 1-866-591-5777.

For additional information about adverse drug experience reporting for animal drugs, contact FDA at 1-888-FDA-VETS or http://www.fda.gov/reportanimalae.

CLINICAL PHARMACOLOGY:

Methimazole is an antithyroid drug that acts by blocking the biosynthesis of thyroid hormone in vivo. The primary action is to inhibit binding of iodide to the enzyme thyroid peroxidase, thereby preventing the catalyzed iodination of thyroglobulin and T3 and T4 synthesis.

Methimazole is well absorbed following oral administration. Maximum plasma concentrations are achieved within 1-1 1/2 hours after dosing and methimazole is rapidly eliminated from the blood (T1/2 is approximately 3 hours). Administration of methimazole in a fasted state enhances absorption.

EFFECTIVENESS:

In a US effectiveness field study with 113 cats, the product was considered effective if both the TT4 concentration was ≤ 4.0 mcg/dL, and the Investigator's clinical assessment documented clinical improvement. Of the 105 evaluable cases, 64 (61%) were considered treatment successes. The decrease in TT4 concentration was significant from the pre-enrollment visit to the Day 42 visit. A TT4 of ≤ 4.0 mcg/dL occurred in 59.1% and 61.9% of cats on Day 21 and Day 42, respectively. Investigators assessed 91.8% and 87.6% of cats as clinically improved on Days 21 and 42, respectively.

In the extended use phase of the US effectiveness field study with 101 cats, effectiveness was based on a combination of lnvestigator's clinical assessment, maintenance of TT4 concentrations at or near the laboratory reference range of 0.8-4.0 mcg/dL, and the presence or absence of adverse reactions. Mean TT4 concentrations were within or near the laboratory reference range during the first four quarterly visits. At the first quarterly visit, Investigators categorized 80.9% of cats as stable or improved relative to their baseline assessment. By the fourth quarterly visit, 75.8% were deemed to be stable or improved.

The average maintenance dose required in the extended use phase was 2.5 mg twice daily, with a minimum of 2.5 mg per cat and a maximum of 15 mg per cat on a daily basis.

ANIMAL SAFETY:

ANIMAL SAFETY STUDIES: In a 12-week safety study, healthy young cats were dosed with 0, 10, 20, and 30 mg methimazole per day, divided into two doses. Cats in all treated, groups experienced anorexia, vomiting, loose stool and lethargy. Cats in the 20 and 30 mg/day groups also had facial excoriations, pruritus, and lymphadenopathy. The following hematological changes were seen: neutropenia, lymphopenia, anemia, and thrombocytopenia. The following biochemical changes were seen: increased globulin, increased magnesium, increased blood urea nitrogen, increased creatinine and decreased phosphorus. There was a dose-dependent occurrence of antinuclear antibodies. Most of the clinical pathology changes were mild in nature. One cat dosed with 20 mg/day experienced a six-fold increase in ALT during the study. This cat had loose stool, but was otherwise healthy throughout the study. Hepatomegaly was seen in this cat at necropsy and the histopathological examination was comparable to other treated cats with hepatomegaly and normal ALT.

Gross necropsy findings in all treated groups included hepatomegaly, thymus atrophy and thyroid hyperplasia and darkening. Some treated males had delayed maturation of the testes. The 30 mg/day dose was poorly tolerated and resulted in the clinical deterioration and euthanasia of four of the six cats in that group. Two of the cats showed signs of immune-mediated hemolytic anemia, thrombocytopenia and severe clinical deterioration. One had been on the drug for 34 days, the other for 9 weeks. The drug was discontinued in a third cat treated with 30 mg/day while it received supportive care. It was euthanized on day 55 after becoming anorexic. This cat had anemia (HCT 21.6%) and red blood cell agglutination. Necropsy showed inflammation of the muscular layer of the stomach and a small erosion in the stomach. A fourth cat treated with 30 mg/day was euthanized after several days of anorexia when the decision was made to discontinue dosing in this group. All 30 mg/day cats that died had generalized lymphadenopathy. Necropsies revealed reactive lymph nodes and varying degrees of inflammation throughout the body. The remaining 2 cats in the 30 mg/day group were taken off methimazole at week 9 and fully recovered.

STORAGE INFORMATION:

Store at controlled room temperature 25°C (77°F) with excursions between 15°-30°C (59°-86°F) permitted.

Keep the container tightly closed.

HOW SUPPLIED:

Felanorm is available at 5mg/mL in bottles containing 30 or 100mL with 1mL dosing syringe.

Approved by FDA under ANADA # 200-771

TAKE TIME

OBSERVE LABEL
DIRECTIONS

Manufactured by:

Norbrook Laboratories Limited
Newry, Co. Down, BT35 6QQ, Northern Ireland
Felanorm® is a trademark of Norbrook Laboratories Limited
US Patent Numbers: 10,045,967, US 11,123,327 and US 11,738,005
Rev. 08/2024
317670I04
Norbrook®

INSTRUCTIONS FOR USE

Instructions for Preparing a Dose of Felanorm (methimazole) Oral Solution

To draw up a dose, carefully follow these instructions. Prior to preparing a dose, carefully read the Special precautions to be taken when administering Felanorm in the Information for Cat Owners.

1. Always wear protective single use, impermeable (e.g., latex or nitrile) gloves when preparing and administering the cat's dose of this medicine.
2. Push and turn the screw cap to open the bottle. Attach the dosing syringe to the bottle by gently pushing the end onto the top of the bottle.
  Note: Always cap the bottle after use.
3. Check that the plunger of the oral dosing syringe (included with the product bottle) is pushed all the way down.
4. Turn the bottle/syringe upside down. Pull the plunger back/down until the oral dosing syringe fills with medicine.
5. Carefully expel any large bubbles by pushing and pulling the plunger a few times with the bottle upside down. The presence of a few tiny bubbles is not important for dosing accuracy.
6. Fill the syringe with the dose of medicine prescribed by your veterinarian by pulling the plunger back/down slowly. The scale on the oral dosing syringe corresponds to the milligram (mg) dose. The end of plunger nearest the tip of the syringe should be level with the measurement (line) corresponding to the correct mg dose.
7. Turn the bottle right way up and with a twisting movement, separate the dosing syringe from the bottle.
  Note: If the prescribed dose is more than one syringe-full (5 mg or 1 milliliter (mL) of solution), you will need to reload the syringe with additional medication to provide the full dose. In this case, the total dose will need to be given via multiple fillings of the dosing syringe. For instance, if the dose is 7.5 mg, then you will need to give one syringe-full (5 mg) plus an additional 2.5 mg to provide the full dose.
8. Push the plunger to empty the content of the syringe directly in the cat's mouth.

The product should be administered slowly and gently, allowing the cat to swallow the product. The product is administered by pushing it out of the syringe with the syringe plunger.

Following administration, any residual product remaining on the tip of the dosing syringe should be wiped clean with a disposable item (napkin, paper towel, or tissue). The contaminated item (napkin, paper towel, or tissue) should be disposed of immediately in a trash receptacle. To avoid contamination of the product bottle, the dosing syringe should be rinsed externally, cleaned, and dried between doses and between individual fillings (when multiple fillings of the dosing syringe are needed to provide a single dose). The bottle cap should be screwed back on the product bottle tightly, and the dosing syringe should be stored with the product bottle in the original carton.

Wash your hands with soap and water after administration to avoid exposure to the drug.

Keep out of reach of children.

INFORMATION FOR OWNERS/CAREGIVERS

Felanorm (methimazole) oral solution

Information for Cat Owners

This summary contains important information about Felanorm. You should read this information before starting your cat on Felanorm and review it each time the prescription is refilled. This sheet is provided only as a summary and does not take the place of instructions from your veterinarian. Talk to your veterinarian if you do not understand any of this information or if you want to know more about Felanorm.

What is Felanorm?

Felanorm is a prescription oral solution containing methimazole and is used for the treatment of hyperthyroidism in cats.

Hyperthyroidism occurs when the thyroid gland over-produces thyroid hormone and is a lifelong condition that requires treatment. Felanorm reduces the production of thyroid hormone. Common signs of hyperthyroidism include weight loss, and an increase in appetite, thirst, and urination. Other signs may include vomiting, diarrhea, hyperactivity, and unkempt coat.

What kind of results can I expect when my cat takes Felanorm for the control of hyperthyroidism?

Felanorm controls hyperthyroidism but does not cure the disease. It may take several weeks for the medication to normalize the thyroid hormone levels. Improvement in signs may include: weight gain or cessation of weight loss, a decrease in excessive appetite, water consumption, and urination, and a decrease in vomiting, diarrhea, and hyperactivity. Your veterinarian will evaluate your cat several weeks after starting treatment and on a regular basis thereafter to determine if dose adjustments are needed. Dose adjustment should only be carried out in consultation with your veterinarian.

What cats should not take Felanorm?

Your cat should not be given Felanorm if s/he:

- Is hypersensitive to methimazole
- Has been diagnosed with primary liver disease or kidney failure
- Has been diagnosed with an autoimmune disease
- Has been diagnosed with a blood disorder (such as anemia or low blood cell counts) or a clotting disorder
- Is pregnant or nursing

What to discuss with your veterinarian before giving Felanorm to your cat.

Tell your veterinarian about:

- Any serious disease or health conditions your cat has had
- Any previous treatments for hyperthyroidism, including methimazole treatment or radioactive iodine, and any side effects related to those treatments
- Any allergies that your cat has now or has had
- All medications that you are giving your cat or plan to give your cat, including those you can get without prescription (over-the-counter) and any dietary supplements
- If you plan to breed your cat, or if your cat is pregnant or nursing

Talk to your veterinarian about:

- What tests might be done before Felanorm is prescribed
- The potential side effects your cat may experience while taking Felanorm
- How often your cat may need to be examined by your veterinarian
- The risks and benefits of using Felanorm, including human user safety risks

What are the possible side effects that may occur in my cat during therapy with Felanorm?

Felanorm, like all other drugs, may cause side effects in individual cats. These are normally mild, but serious side effects have been reported in cats taking methimazole. Serious side effects can, in rare situations, result in death. It is important to stop the medication and contact your veterinarian immediately if you think your cat may have a medical problem or side effect while on Felanorm.

Possible side effects include loss of appetite, lethargy, vomiting, diarrhea/loose stool, head and facial itchiness or swelling, skin lesions, weight loss, elevated liver enzymes, elevated kidney enzymes, abnormal vocalization, and low counts of red cells, white cells, and platelets. Methimazole may cause your cat to bleed or bruise more easily. In some cases, patients recovered after side effects from methimazole were recognized, methimazole was withdrawn, and veterinary care was administered. In some cases, death (or euthanasia) was the outcome of the side effects.

To report suspected adverse drug events, for technical assistance or to obtain a copy of the Safety Data Sheet (SDS), contact Norbrook at 1-866-591-5777. For additional information about adverse drug experience reporting for animal drugs, contact FDA at 1-888-FDA-VETS or http://www.fda.gov/reportanimalae.

Felanorm should only be given to cats.

People should not take Felanorm. Keep Felanorm and all medication out of reach of children. Call your physician immediately if you accidentally swallow Felanorm.

How to give Felanorm to your cat.

Felanorm should be given as prescribed by your veterinarian and according to your veterinarian's instructions. Your veterinarian will tell you what amount of Felanorm is right for your cat. Whenever possible, you should administer Felanorm on a consistent schedule with regard to time of day. Do not change the way you give Felanorm to your cat without first speaking with your veterinarian. If a dose is missed, resume dosing based on your cat's regular dosing schedule. Do not give double the dose the next time. If your cat is due to have a monitoring blood test within a couple of days of missing a dose, make sure you tell your veterinarian as it could affect the blood results.

Advice on Correct Administration.

See Instructions for Preparing a Dose of Felanorm (methimazole) Oral Solution.

How to Store Felanorm.

Felanorm should be stored in the original container at room temperature (77°F), however temperatures between 59°-86°F are permitted.

Special precautions to be taken when administering Felanorm.

Methimazole can cause or increase the risk of birth defects in human babies.

Always wear protective single use, impermeable (e.g., latex or nitrile) gloves when administering Felanorm or to prevent direct contact with litter, feces, urine, or vomit of treated cats. Wash your hands with soap and water after administration of Felanorm or after contact with the litter of treated cats to avoid exposure to Felanorm. This is especially important if you are pregnant, become pregnant, are nursing, or have an endocrine disorder that could be impacted by Felanorm.

Avoid skin and oral exposure, including hand-to-mouth contact. Wash any spillages or splatter from the skin immediately. Do not eat, drink, smoke/vape, or use smokeless tobacco while handling the product or used litter. In the event of accidental ingestion, seek medical advice immediately and show the product label to the physician.

Felanorm may cause skin or eye irritation. Avoid eye contact, including hand-to-eye contact. In case of accidental eye contact, rinse eyes immediately with clean running water. If irritation develops, seek medical advice.

Can Felanorm be given with other medications?

Interactions with certain medications are possible. Always tell your veterinarian about all medications, including those you can get without a prescription (over-the-counter), that you have given your cat in the past and all medications that you are planning to give with Felanorm.

What can I do if my cat gets more than the prescribed amount of Felanorm?

Contact your veterinarian immediately if your cat gets more than the prescribed amount of Felanorm.

What else should I know about Felanorm?

This sheet provides a summary of information about Felanorm. If you have any questions or concerns about Felanorm or hyperthyroidism in cats, talk to your veterinarian.

As with all prescribed medications, Felanorm should only be given to the cat and condition for which it was prescribed, at the prescribed dose, and as directed by your veterinarian.

Principal Display Panel – 100 mL Carton Label

NDC 55529-170-02

5 mg of methimazole/mL

Felanorm®
(methimazole)

Oral Solution

5 mg of
methimazole/mL

100 mL

For oral use in cats only

CAUTION: Federal law restricts this drug to use by
or on the order of a licensed veterinarian.

Approved by FDA under ANADA # 200-771

Norbrook®